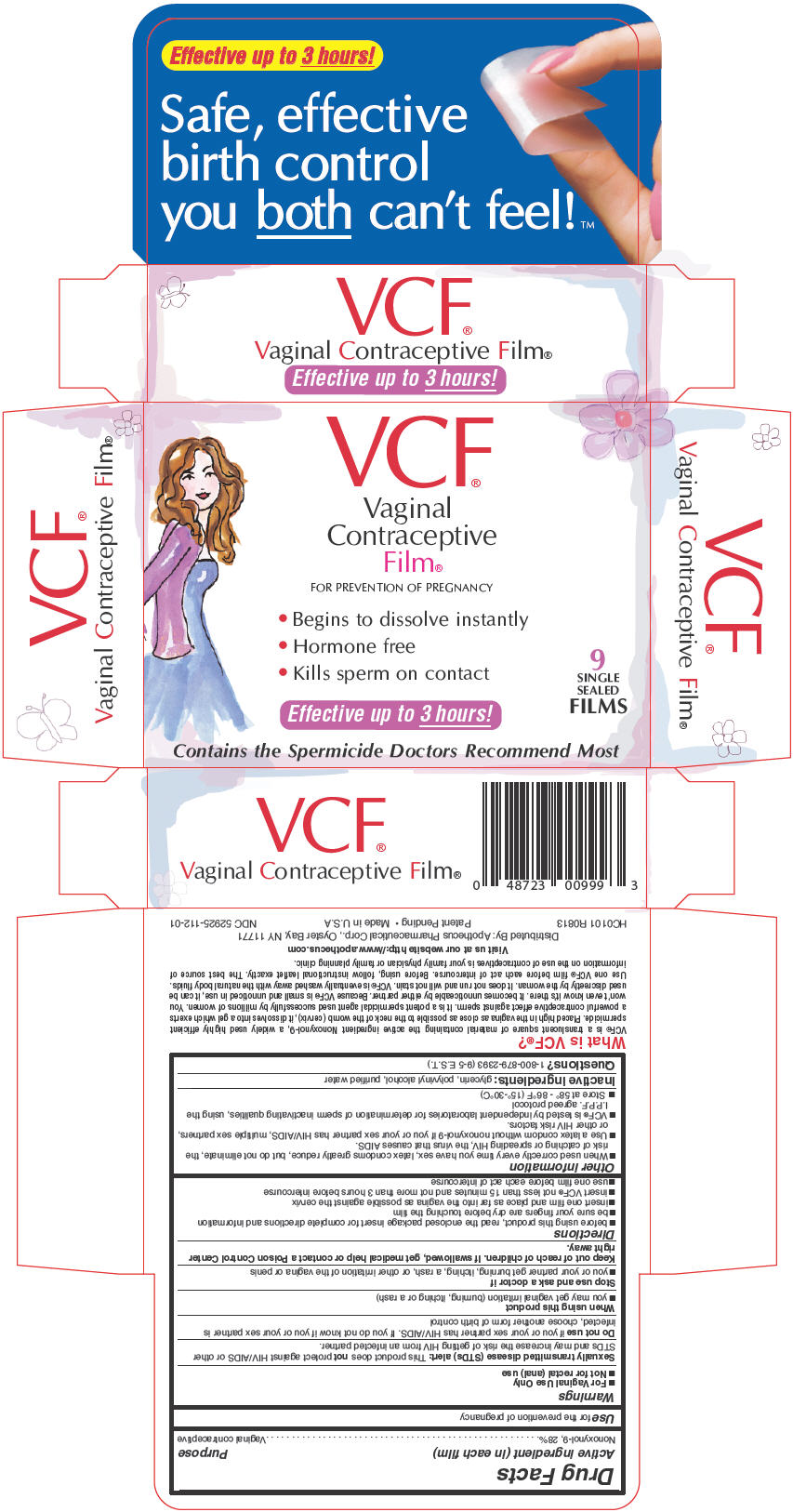 DRUG LABEL: VCF CONTRACEPTIVE
NDC: 52925-112 | Form: FILM, SOLUBLE
Manufacturer: APOTHECUS PHARMACEUTICAL CORP.
Category: otc | Type: HUMAN OTC DRUG LABEL
Date: 20251212

ACTIVE INGREDIENTS: NONOXYNOL-9 280 mg/1 1
INACTIVE INGREDIENTS: GLYCERIN; POLYVINYL ALCOHOL, UNSPECIFIED; WATER

VCF® VAGINAL CONTRACEPTIVE FILM®

Drug Facts

Active ingredient (in each film)

Nonoxynol-9, 28%

Purpose

Vaginal contraceptive

Use

for the prevention of pregnancy

Warnings

- For Vaginal Use Only
- Not for rectal (anal) use

Sexually transmitted disease (STDs) alert

This product does not protect against HIV/AIDS or other STDs and may increase the risk of getting HIV from an infected partner.

Do not use if you or your sex partner has HIV/AIDS. If you do not know if you or your sex partner is infected, choose another form of birth control

When using this product

- you may get vaginal irritation (burning, itching or a rash)

Stop use and ask a doctor if

- you or your partner get burning, itching, a rash, or other irritation of the vagina or penis

Keep out of reach of children. If swallowed, get medical help or contact a Poison Control Center right away.

Directions

- before using this product, read the enclosed package insert for complete directions and information
- be sure your fingers are dry before touching the film
- insert one film and place as far into the vagina as possible against the cervix
- insert VCF® not less than 15 minutes and not more than 3 hours before intercourse
- use one film before each act of intercourse

Other information

- When used correctly every time you have sex, latex condoms greatly reduce, but do not eliminate, the risk of catching or spreading HIV, the virus that causes AIDS.
- Use a latex condom without nonoxynol-9 if you or your sex partner has HIV/AIDS, multiple sex partners, or other HIV risk factors.
- VCF® is tested by independent laboratories for determination of sperm inactivating qualities, using the I.P.P.F. agreed protocol
- Store at 58° - 86°F (15°-30°C)

Inactive ingredients

glycerin, polyvinyl alcohol, purified water

Questions?

1-800-879-2393 (9-5 E.S.T.)

Distributed By: Apothecus Pharmaceutical Corp., Oyster Bay, NY 11771

PRINCIPAL DISPLAY PANEL - 9 x 1 Film Pouch Box

VCF®
Vaginal
Contraceptive
Film®
FOR PREVENTION OF PREGNANCY

- Begins to dissolve instantly
- Hormone free
- Kills sperm on contact

Effective up to 3 hours!

9
SINGLE
SEALED
FILMS

Contains the Spermicide Doctors Recommend Most